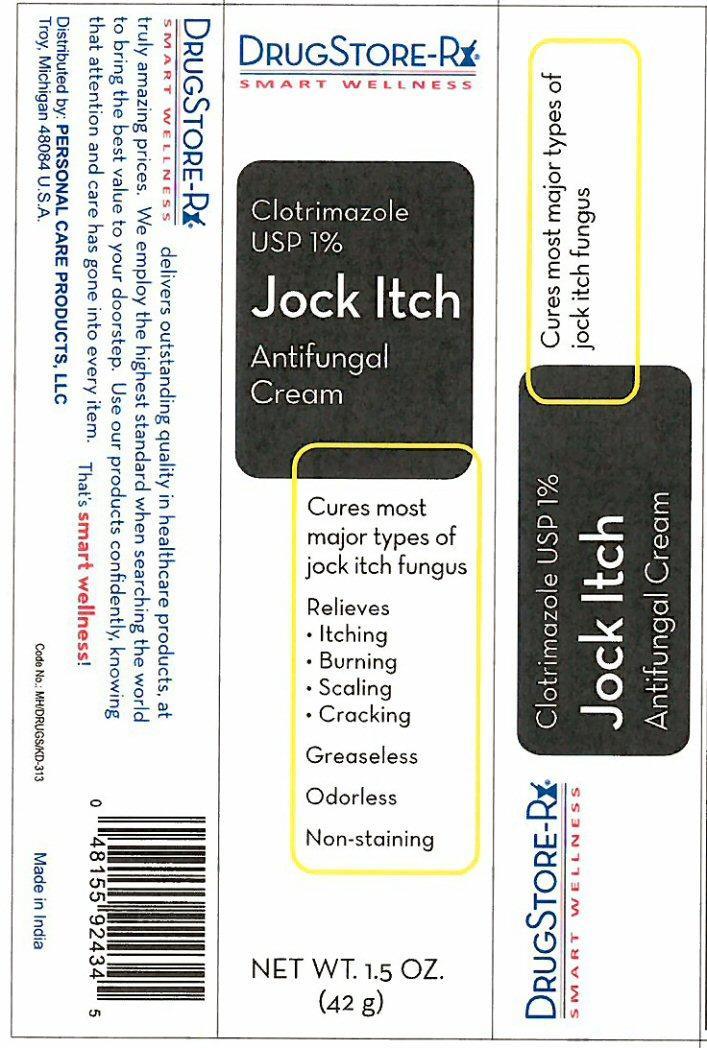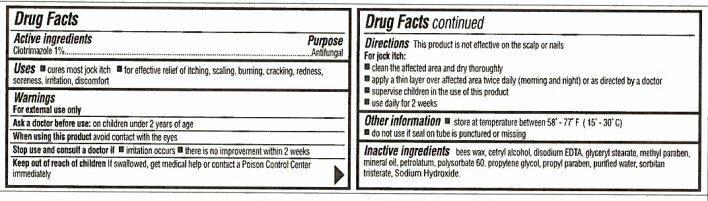 DRUG LABEL: Jock Itch
NDC: 29500-2434 | Form: CREAM
Manufacturer: Personal Care Products, Inc.
Category: otc | Type: HUMAN OTC DRUG LABEL
Date: 20200723

ACTIVE INGREDIENTS: CLOTRIMAZOLE 420 mg/42 g
INACTIVE INGREDIENTS: YELLOW WAX; CETYL ALCOHOL; EDETATE DISODIUM; GLYCERYL MONOSTEARATE; METHYLPARABEN; MINERAL OIL; PETROLATUM; POLYSORBATE 60; PROPYLENE GLYCOL; PROPYLPARABEN; WATER; SORBITAN TRISTEARATE; SODIUM HYDROXIDE

Active ingredients

Drug Facts

Clotrimazole 1%

Purpose

Antifungal

Keep out of reach of children. If swallowed, get medical help or contact a Poison Control Center immediately.

Uses

- cures most jock itch
- for effective relief of itching, scaling, burning, cracking, redness, soreness, irritation, discomfort

Warnings

For external use only

Ask a doctor before use: on children under 2 years of age

When using this product avoid contact with the eyes

Stop use and consult a doctor if

- irritation occurs
- there is no improvement within 2 weeks

Directions

This product is not effective on the scalp or nails

For jock itch:

- clean the affected area and dry thoroughly
- apply a thin layer over affected area twice daily (morning and night) or as directed by a doctor
- supervise children in the use of this product
- use daily for 2 weeks

Other information

- store at temperature between 58° - 77° F (15° - 30° C)
- do not use if seal on tube is punctured or missing

Inactive ingredients

bees wax, cetryl alcohol, disodium EDTA, glyceryl stearate, methyl paraben, mineral oil, petrolatum, polysorbate 60, propylene glycol, propyl paraben, purified water, sorbitan tristerate, Sodium Hydroxide.

Product Label

DRUGSTORE-Rx
SMART WELLNESS
Clotrimazole USP 1%
Jock Itch
Antifungal Cream
Cures most types of jock itch fungus
Relieves

- Itching
- Burning
- Scaling
- Cracking

Greaseless

Odorless
Non-staining
NET WT. 1.5 OZ. (42 g)
DRUGSTORE-Rx
SMART WELLNESS delivers outstanding quality in healthcare products, at truly amazing prices. We employ the highest standard when searching the world to bring the best value to your doorstep. Use our products confidently, knowing that attention and care has gone into every item. That's smart wellness!
Distributed by: PERSONAL CARE PRODUCTS, LLC
Troy, Michigan 48084 U.S.A.
Code No. MH/DRUGS/KD-313 Made in India